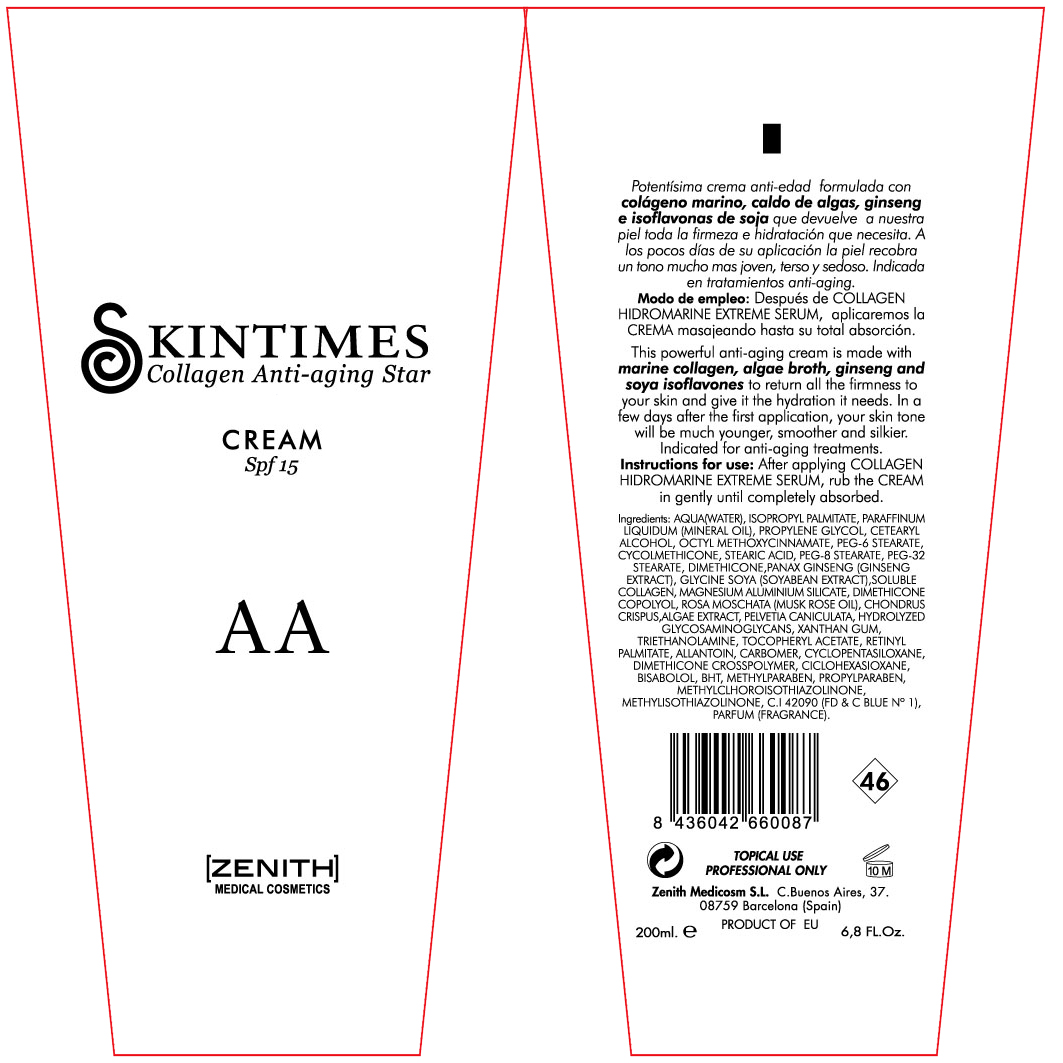 DRUG LABEL: Anti Aging
NDC: 42248-113 | Form: CREAM
Manufacturer: Zenith Medicosm SL
Category: otc | Type: HUMAN OTC DRUG LABEL
Date: 20120121

ACTIVE INGREDIENTS: OCTINOXATE 15 mL/200 mL
INACTIVE INGREDIENTS: MAGNESIUM ALUMINUM SILICATE; PROPYLPARABEN; ALPHA-TOCOPHEROL ACETATE; DIMETHICONE; XANTHAN GUM; ROSA MOSCHATA OIL; WATER; MINERAL OIL; CETOSTEARYL ALCOHOL; PEG-8 STEARATE; TROLAMINE; SOYBEAN; CHONDRUS CRISPUS; BUTYLATED HYDROXYTOLUENE; DIMETHICONE 20; CARBOMER 934; HYDROLYZED GLYCOSAMINOGLYCANS (BOVINE; 50000 MW); METHYLCHLOROISOTHIAZOLINONE; METHYLPARABEN; COLLAGEN, SOLUBLE, FISH SKIN; ISOPROPYL PALMITATE; PEG-6 STEARATE; PEG-32 STEARATE; STEARIC ACID; PANAX GINSENG FRUIT; FUCUS VESICULOSUS; PELVETIA CANALICULATA; CYCLOMETHICONE; VITAMIN A PALMITATE; ALLANTOIN; CYCLOMETHICONE 5; LEVOMENOL; PROPYLENE GLYCOL; METHYLISOTHIAZOLINONE; CYCLOMETHICONE 6; FD&C BLUE NO. 1

Drug Facts

Active Ingredient

Octinoxate 7.5%

Description

This powerful anti-aging cream is made with marine collagen, algae broth, ginseng and soya isoflavones to return all the firmness to your skin and give it the hydration it needs. In a few days after first application, your skin tone will be much younger, smoother and silkier.Indicated for anti-aging treatments.

200ml. 6.8Fl.Oz

Warning

TOPICAL USE

PROFESSIONAL USE

INDICATIONS AND USAGE

After applying COLLAGEN HIDROMARINE EXTREME SERUM, rub the CREAM in gently until completely absorbed.